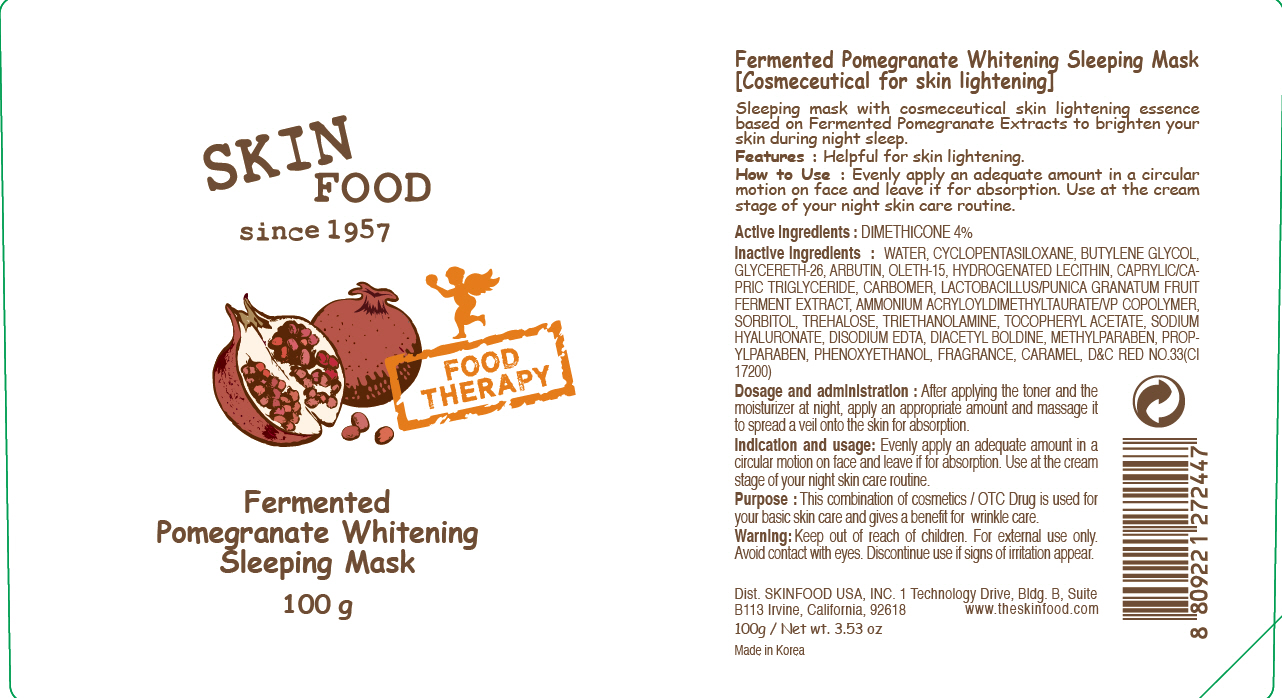 DRUG LABEL: FERMENTED POMEGRANTE WHITENING SLEEPING MASK
NDC: 76214-022 | Form: PATCH
Manufacturer: SKINFOOD CO., LTD.
Category: otc | Type: HUMAN OTC DRUG LABEL
Date: 20110922

ACTIVE INGREDIENTS: DIMETHICONE 4 g/100 g
INACTIVE INGREDIENTS: WATER; CYCLOMETHICONE 5; BUTYLENE GLYCOL; GLYCERETH-26; ARBUTIN; HYDROGENATED SOYBEAN LECITHIN; MEDIUM-CHAIN TRIGLYCERIDES; PHENOXYETHANOL; METHYLPARABEN; SORBITOL; TREHALOSE; TROLAMINE; PROPYLPARABEN; HYALURONATE SODIUM; CARAMEL; EDETATE DISODIUM

Drug Facts

Active ingredient: DIMETHICONE 4%

Inactive ingredients:
WATER, CYCLOPENTASILOXANE, BUTYLENE GLYCOL, GLYCERETH-26, ARBUTIN, OLETH-15, HYDROGENATED LECITHIN, CAPRYLIC/CAPRIC TRIGLYCERIDE, CARBOMER, LACTOBACILLUS/PUNICA GRANATUM FRUIT FERMENT EXTRACT, AMMONIUM ACRYLOYLDIMETHYLTAURATE/VP COPOLYMER, SORBITOL, TREHALOSE, TRIETHANOLAMINE, TOCOPHERYL ACETATE, SODIUM HYALURONATE, DISODIUM EDTA, DIACETYL BOLDINE, METHYLPARABEN, PROPYLPARABEN, PHENOXYETHANOL, FRAGRANCE, CARAMEL

PURPOSE

Purpose: This combination of cosmetics / OTC Drug is used for your basic skin care and gives a benefit for brightning care.

Warnings:
For external use only.
Avoid contact with eyes.
Discontinue use if signs of irritation appear.

Keep out of reach of children:
Keep out of reach of children.

Indication and usage:
Evenly apply an adequate amount in a circular motion on face and leave if for absorption.
Use at the cream stage of your night skin care routine.

Dosage and administration:
After applying the toner and the moisturizer at night, apply an appropriate amount and massage it to spread a veil onto the skin for absorption.